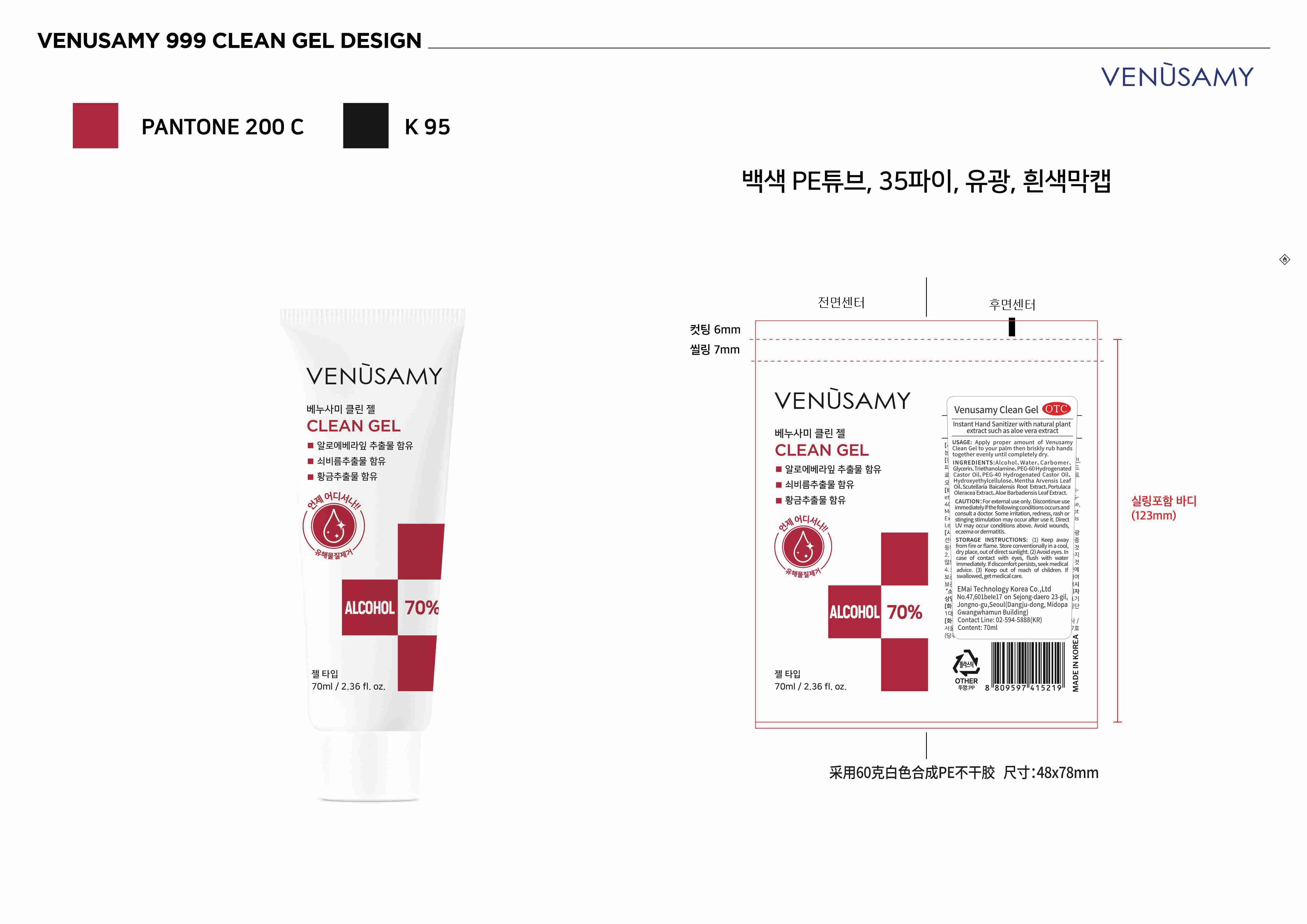 DRUG LABEL: Venusamy clean gel
NDC: 68632-002 | Form: GEL
Manufacturer: E-LINK GLOBAL TECH CO., LIMITED
Category: otc | Type: HUMAN OTC DRUG LABEL
Date: 20200630

ACTIVE INGREDIENTS: ALCOHOL 49 mL/70 mL
INACTIVE INGREDIENTS: MENTHA ARVENSIS LEAF OIL; ALOE VERA LEAF; CARBOMER HOMOPOLYMER, UNSPECIFIED TYPE; TROLAMINE; HYDROXYETHYL CELLULOSE, UNSPECIFIED; WATER; GLYCERIN; POLYOXYL 60 HYDROGENATED CASTOR OIL; POLYOXYL 40 HYDROGENATED CASTOR OIL; SCUTELLARIA BAICALENSIS ROOT; PURSLANE

DOSAGE AND ADMINISTRATION

Store conventionally in a cool,dry place, out of direct sunlight.

INACTIVE INGREDIENT

Water. Carbomer.Glycerin. Triethanolamine. PEG 60 Hydrogenated Castor Oil、PEG-40 Hydrogenated Castor 0il Hydroxyethylcellulose. Mentha Arvensis Leaf oil、Scutellaria Baicalensis Root Extract. Portulaca Oleracea Extract. Aloe Barbadensis Leaf Extract.

INDICATIONS AND USAGE

Apply proper amount of Venusamy Clean Gel to your palm then briskly rub hands together evenly until completely dry.

ACTIVE INGREDIENT

Alcohol

keep out of reach of children

PURPOSE

Disinfection
Sterilization
No Rinseing

WARNINGS

For external use only. Discontinue use immediately ifthe following conditions occurs and consult a doctor. Some iritation, redness, rash or stinging stimulation may occur after use it. Direct UV may occur conditions above. Avoid wounds,eczema or dermatitis.